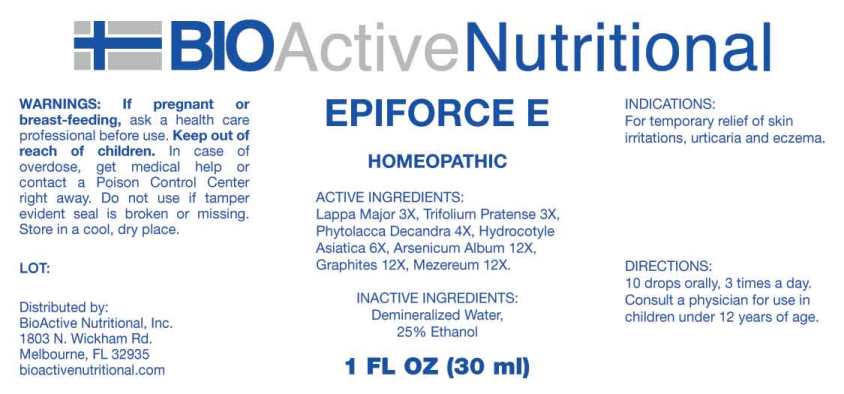 DRUG LABEL: Epiforce E
NDC: 43857-0570 | Form: LIQUID
Manufacturer: BioActive Nutritional, Inc.
Category: homeopathic | Type: HUMAN OTC DRUG LABEL
Date: 20230721

ACTIVE INGREDIENTS: ARCTIUM LAPPA ROOT 3 [hp_X]/1 mL; TRIFOLIUM PRATENSE FLOWER 3 [hp_X]/1 mL; PHYTOLACCA AMERICANA ROOT 4 [hp_X]/1 mL; CENTELLA ASIATICA WHOLE 6 [hp_X]/1 mL; ARSENIC TRIOXIDE 12 [hp_X]/1 mL; GRAPHITE 12 [hp_X]/1 mL; DAPHNE MEZEREUM BARK 12 [hp_X]/1 mL
INACTIVE INGREDIENTS: WATER; ALCOHOL

DRUG FACTS:

ACTIVE INGREDIENTS:

Lappa Major 3X, Trifolium Pratense 3X, Phytolacca Decandra 4X, Hydrocotyle Asiatica 6X, Arsenicum Album 12X, Graphites 12X, Mezereum 12X.

INDICATIONS:

For temporary relief of skin irritations, urticaria and eczema.

WARNINGS:

If pregnant or breast-feeding, ask a health care professional before use.

Keep out of reach of children. In case of overdose, get medical help or contact a Poison Control Center right away.

Do not use if tamper evident seal is broken or missing.

Store in a cool, dry place.

Keep out of reach of children. In case of overdose, get medical help or contact a Poison Control Center right away.

DIRECTIONS:

10 drops orally, 3 times a day. Consult a physician for use in children under 12 years of age.

INDICATIONS:

For temporary relief of skin irritations, urticaria and eczema.

INACTIVE INGREDIENTS:

Demineralized Water, 25% Ethanol

QUESTIONS:

Distributed by:
BioActive Nutritional, Inc.
1803 N. Wickham Rd.
Melbourne, FL 32935
bioactivenutritional.com

PACKAGE LABEL DISPLAY:

BIOActive Nutritional

EPIFORCE E

HOMEOPATHIC

1 FL OZ (30 ml)